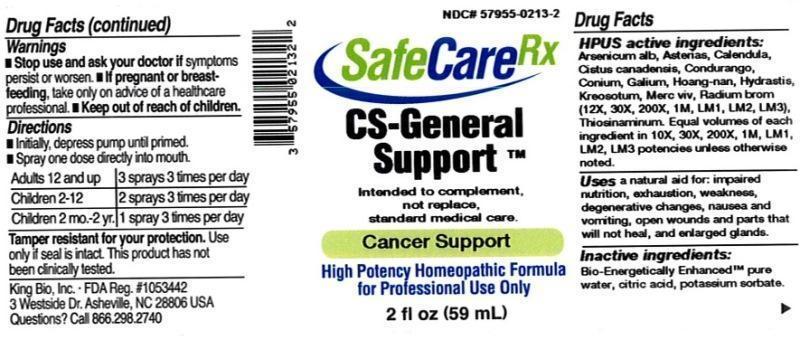 DRUG LABEL: CS General Support
NDC: 57955-0213 | Form: LIQUID
Manufacturer: King Bio Inc.
Category: homeopathic | Type: HUMAN OTC DRUG LABEL
Date: 20150602

ACTIVE INGREDIENTS: ARSENIC TRIOXIDE 10 [hp_X]/59 mL; ASTERIAS RUBENS 10 [hp_X]/59 mL; CALENDULA OFFICINALIS FLOWERING TOP 10 [hp_X]/59 mL; HELIANTHEMUM CANADENSE 10 [hp_X]/59 mL; MARSDENIA CONDURANGO BARK 10 [hp_X]/59 mL; CONIUM MACULATUM FLOWERING TOP 10 [hp_X]/59 mL; GALLIC ACID MONOHYDRATE 10 [hp_X]/59 mL; STRYCHNOS WALLICHIANA BARK 10 [hp_X]/59 mL; GOLDENSEAL 10 [hp_X]/59 mL; WOOD CREOSOTE 10 [hp_X]/59 mL; MERCURY 10 [hp_X]/59 mL; RADIUM BROMIDE 12 [hp_X]/59 mL; ALLYLTHIOUREA 10 [hp_X]/59 mL
INACTIVE INGREDIENTS: WATER; ANHYDROUS CITRIC ACID; POTASSIUM SORBATE

CS General Support™

ACTIVE INGREDIENT

Drug Facts__________________________________________________________________________________________________________

HPUS active ingredients: Arsenicum album, Asterias rubens, Calendula officinalis, Cistus canadensis, Condurango, Conium maculatum, Gallicum acidum, Hoanga-Nan, Hydrastis canadensis, Kreosotum, Mercurius vivus, Radium bromatum (12X, 30X, 200X, 1M, LM1, LM2, LM3) Thiosinaminum. Equal volumes of each ingredient in 10X, 30X, 200X, 1M, LM1, LM2, LM3 potencies unless otherwise noted.

INDICATIONS AND USAGE

Uses a natural aid for: impaired nutrition, exhaustion, weakness, degenerative changes, nausea and vomiting, open wounds and parts that will not heal, and enlarged glands.

Inactive Ingredients:

Bio-Energetically Enhanced™ pure water, citric acid and potassium sorbate.

Warnings

- Stop use and ask your doctor if symptoms persist or worsen.
- If pregnant or breast-feeding, take only on advice of a healthcare professional.

- Keep out of reach of children.

Directions

- Initially, depress pump until primed.
- Spray one dose directly into mouth.
- Adults 12 and up: 3 sprays 3 times per day.
- Children 2-12: 2 sprays 3 times per day.
- Children 2 mo.-2 yr: 1 spray 3 times per day.

OTHER SAFETY INFORMATION

Tamper resistant for your protection. Use only if safety seal is intact. This product has not been clinically tested.

Intended to complement, not replace, standard medical care.

PURPOSE

Uses a natural aid for:

- impaired nutrition
- exhaustion
- weakness
- degenerative changes
- nausea and vomiting
- open wounds and parts that will not heal
- enlarged glands